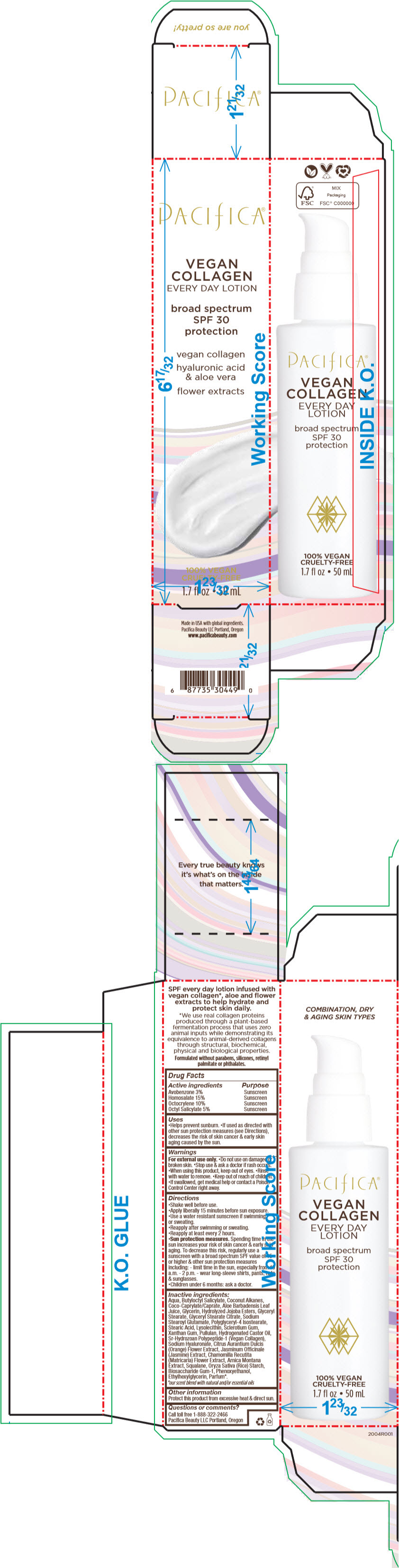 DRUG LABEL: VEGAN COLLAGEN EVERY DAY
NDC: 61197-500 | Form: LOTION
Manufacturer: Pacifica Beauty LLC.
Category: otc | Type: HUMAN OTC DRUG LABEL
Date: 20200622

ACTIVE INGREDIENTS: Avobenzone 30 mg/1 mL; Homosalate 150 mg/1 mL; Octocrylene 100 mg/1 mL; Octisalate 50 mg/1 mL
INACTIVE INGREDIENTS: WATER; BUTYLOCTYL SALICYLATE; COCONUT ALKANES; COCOYL CAPRYLOCAPRATE; ALOE VERA LEAF; GLYCERIN; HYDROLYZED JOJOBA ESTERS (ACID FORM); GLYCERYL MONOSTEARATE; GLYCERYL STEARATE CITRATE; SODIUM STEAROYL GLUTAMATE; POLYGLYCERYL-4 ISOSTEARATE; STEARIC ACID; LYSOPHOSPHATIDYLCHOLINE, SOYBEAN; BETASIZOFIRAN; XANTHAN GUM; PULLULAN; HYDROGENATED CASTOR OIL; HYALURONATE SODIUM; CITRUS SINENSIS FLOWER; JASMINUM OFFICINALE FLOWER; CHAMOMILE; ARNICA MONTANA WHOLE; SQUALANE; STARCH, RICE; BIOSACCHARIDE GUM-1; PHENOXYETHANOL; ETHYLHEXYLGLYCERIN

VEGAN COLLAGEN EVERY DAY

Drug Facts

ACTIVE INGREDIENT

Active ingredients | Purpose
Avobenzone 3% | Sunscreen
Homosalate 15% | Sunscreen
Octocrylene 10% | Sunscreen
Octyl Salicylate 5% | Sunscreen

Uses

- Helps prevent sunburn.
- If used as directed with other sun protection measures (see Directions), decreases the risk of skin cancer & early skin aging caused by the sun.

Warnings

For external use only.

- Do not use on damaged or broken skin.

- Stop use & ask a doctor if rash occurs.

- When using this product, keep out of eyes.
- Rinse with water to remove.

- Keep out of reach of children.
- If swallowed, get medical help or contact a Poison Control Center right away.

Directions

- Shake well before use.
- Apply liberally 15 minutes before sun exposure.
- Use a water resistant sunscreen if swimming or sweating.
- Reapply after swimming or sweating.
- Reapply at least every 2 hours.
- Sun protection measures. Spending time in the sun increases your risk of skin cancer & early skin aging. To decrease this risk, regularly use a sunscreen with a broad spectrum SPF value of 15 or higher & other sun protection measures including:
  - limit time in the sun, especially from 10 a.m. - 2 p.m.
  - wear long-sleeve shirts, pants, hats & sunglasses.
- Children under 6 months: ask a doctor.

Inactive ingredients

Aqua, Butyloctyl Salicylate, Coconut Alkanes, Coco-Caprylate/Caprate, Aloe Barbadensis Leaf Juice, Glycerin, Hydrolyzed Jojoba Esters, Glyceryl Stearate, Glyceryl Stearate Citrate, Sodium Stearoyl Glutamate, Polyglyceryl-4 Isostearate, Stearic Acid, Lysolecithin, Sclerotium Gum, Xanthan Gum, Pullulan, Hydrogenated Castor Oil, Sr-Hydrozoan Polypeptide-1 (Vegan Collagen), Sodium Hyaluronate, Citrus Aurantium Dulcis (Orange) Flower Extract, Jasminum Officinale (Jasmine) Extract, Chamomilla Recutita (Matricaria) Flower Extract, Arnica Montana Extract, Squalane, Oryza Sativa (Rice) Starch, Biosaccharide Gum-1, Phenoxyethanol, Ethylhexylglycerin, Parfum [our scent blend with natural and/or essential oils] .

Other information

Protect this product from excessive heat & direct sun.

Questions or comments?

Call toll free 1-888-322-2466
Pacifica Beauty LLC Portland, Oregon

PRINCIPAL DISPLAY PANEL - 50 mL Bottle Carton

PACIFICA®

VEGAN
COLLAGEN
EVERY DAY LOTION

broad spectrum
SPF 30
protection

vegan collagen

hyaluronic acid
& aloe vera

flower extracts

100% VEGAN
CRUELTY-FREE

1.7 fl oz • 50 mL